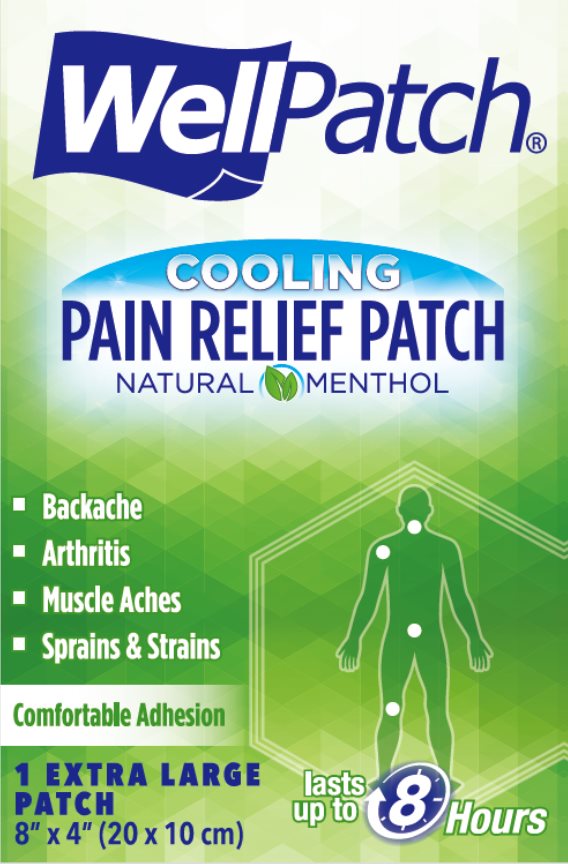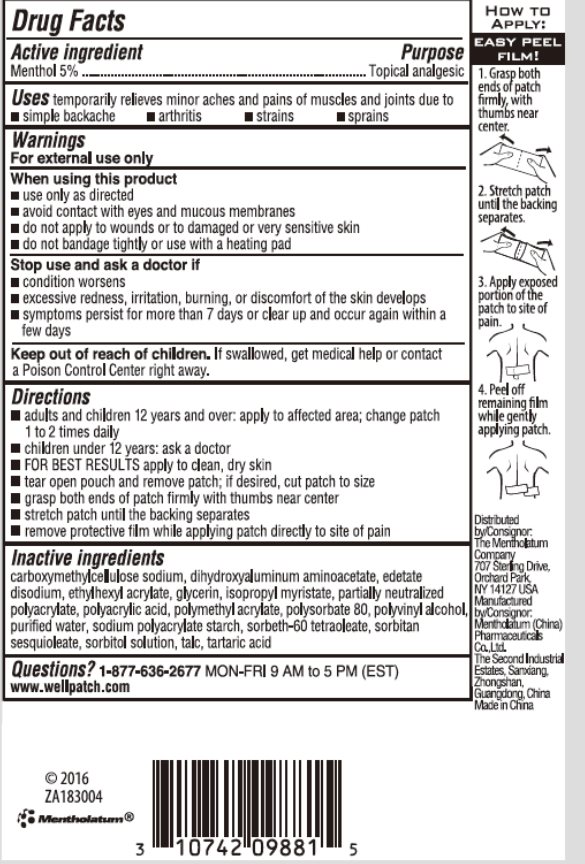 DRUG LABEL: WellPatch Cooling Pain Relief
NDC: 10742-8125 | Form: PATCH
Manufacturer: The Mentholatum Company
Category: otc | Type: HUMAN OTC DRUG LABEL
Date: 20241217

ACTIVE INGREDIENTS: MENTHOL, UNSPECIFIED FORM 50 mg/1 1
INACTIVE INGREDIENTS: CARBOXYMETHYLCELLULOSE SODIUM, UNSPECIFIED FORM; DIHYDROXYALUMINUM AMINOACETATE; EDETATE DISODIUM; 2-ETHYLHEXYL ACRYLATE; GLYCERIN; ISOPROPYL MYRISTATE; METHYL ACRYLATE; POLYACRYLIC ACID (250000 MW); POLYSORBATE 80; POLYVINYL ALCOHOL, UNSPECIFIED; WATER; SORBITAN SESQUIOLEATE; SORBITOL; TALC; TARTARIC ACID

Drug Facts

Active ingredient

Menthol 5%

Purpose

Menthol - Topical Analgesic

Uses

temporarily relieves minor aches and pains of muscles and joints due to

- simple backache
- arthritis
- strains
- sprains

Warnings

For external use only

When using this product

- use only as directed
- avoid contact with eyes and mucous membranes
- do not apply to wounds or to damaged or very sensitive skin
- do not bandage tightly or use with a heating pad

Stop use and ask a doctor if

- condition worsens
- excessive redness, irritation, burning, or discomfort of the skin develops
- pain persists for more than 7 days
- symptoms clear up and occur again within a few days

Keep out of reach of children.

If swallowed, get medical help or contact a Poison Control Center right away.

Directions

- adults and children 12 years and over: apply to affected area; change patch 1 to 2 times daily
- children under 12 years: ask a doctor
- FOR BEST RESULTS apply to clean, dry skin
- tear open pouch and remove patch; if desired, cut patch to size
- grasp both ends of the patch firmly with thumbs near center
- stretch patch until the backing separates
- remove protective film while applying patch directly to site of pain

Inactive ingredients

carboxymethylcellulose sodium, dihydroxyaluminum aminoacetate, edetate disodium, ethylhexyl acrylate, glycerin, isopropyl myristate, partially neutralized polyacrylate, polyacrylic acid, polymethyl acrylate, polysorbate 80, polyvinyl alcohol, purified water, sodium polyacrylate starch, sorbeth-60 tetraoleate, sorbitan sesquioleate, sorbitol solution, talc, tartaric acid

Questions?

1-877-636-2677 MON - FRI 9AM to 5PM (EST)

www.wellpatch.com